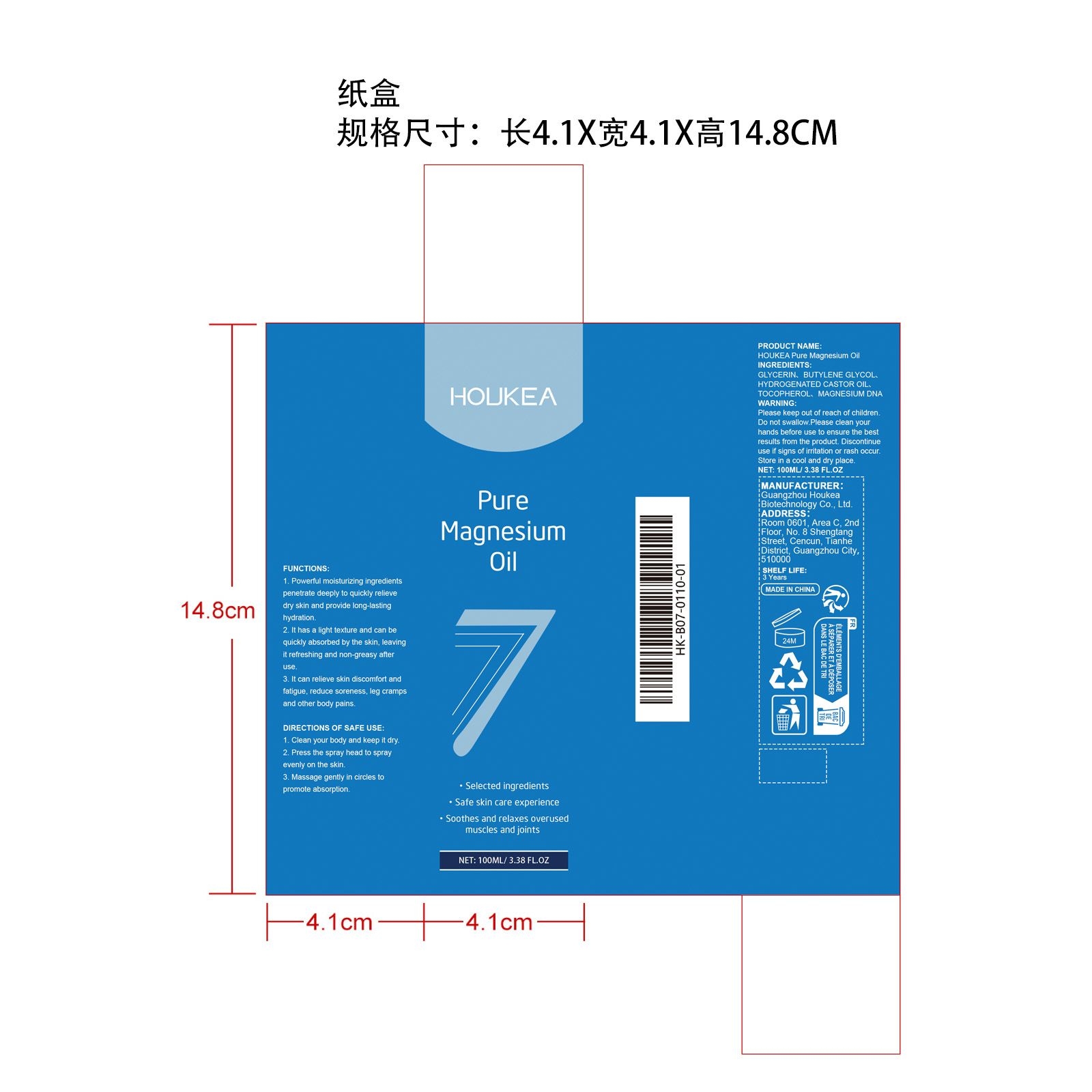 DRUG LABEL: HOUKEA Pure Magnesium Oil
NDC: 84984-005 | Form: OIL
Manufacturer: Guangzhou Houkea Biotechnology Co., Ltd.
Category: otc | Type: HUMAN OTC DRUG LABEL
Date: 20251127

ACTIVE INGREDIENTS: HYDROGENATED CASTOR OIL 0.5 mg/100 mg
INACTIVE INGREDIENTS: BUTYLENE GLYCOL 40 mg/100 mg; GLYCERIN 59.46 mg/100 mg; TOCOPHEROL 0.02 mg/100 mg; MAGNESIUM PCA 0.02 mg/100 mg

ACTIVE INGREDIENT

HYDROGENATED CASTOR OIL

PURPOSE

1. Powerful moisturizing ingredients penetrate deeply to quickly relieve dry skin and provide long-lasting hydration.

2. It has a light texture and can be quickly absorbed by the skin, leaving it refreshing and non-greasy after use.

3. It can relieve skin discomfort and fatigue, reduce soreness, leg cramps and other body pains.

STOP USE

Discontinue use if signs of irritation or rash occur.

DO NOT USE

Discontinue use if signs of irritation or rash occur.

WHEN USING

1. Clean your body and keep it dry.

2. Press the spray head to spray evenly on the skin.

3. Massage gently in circles to promote absorption.

WARNINGS

Please keep out of reach of children. Do not swallow.Please clean your hands before use to ensure the best results from the product. Discontinue use if signs of irritation or rash occur. Store in a cool and dry place.

STORAGE AND HANDLING

Store in a cool and dry place.

KEEP OUT OF REACH OF CHILDREN

Please keep out of reach of children. Do not swallow.

INACTIVE INGREDIENT

GLYCERIN、

BUTYLENE GLYCOL、

TOCOPHEROL、

MAGNESIUM DNA